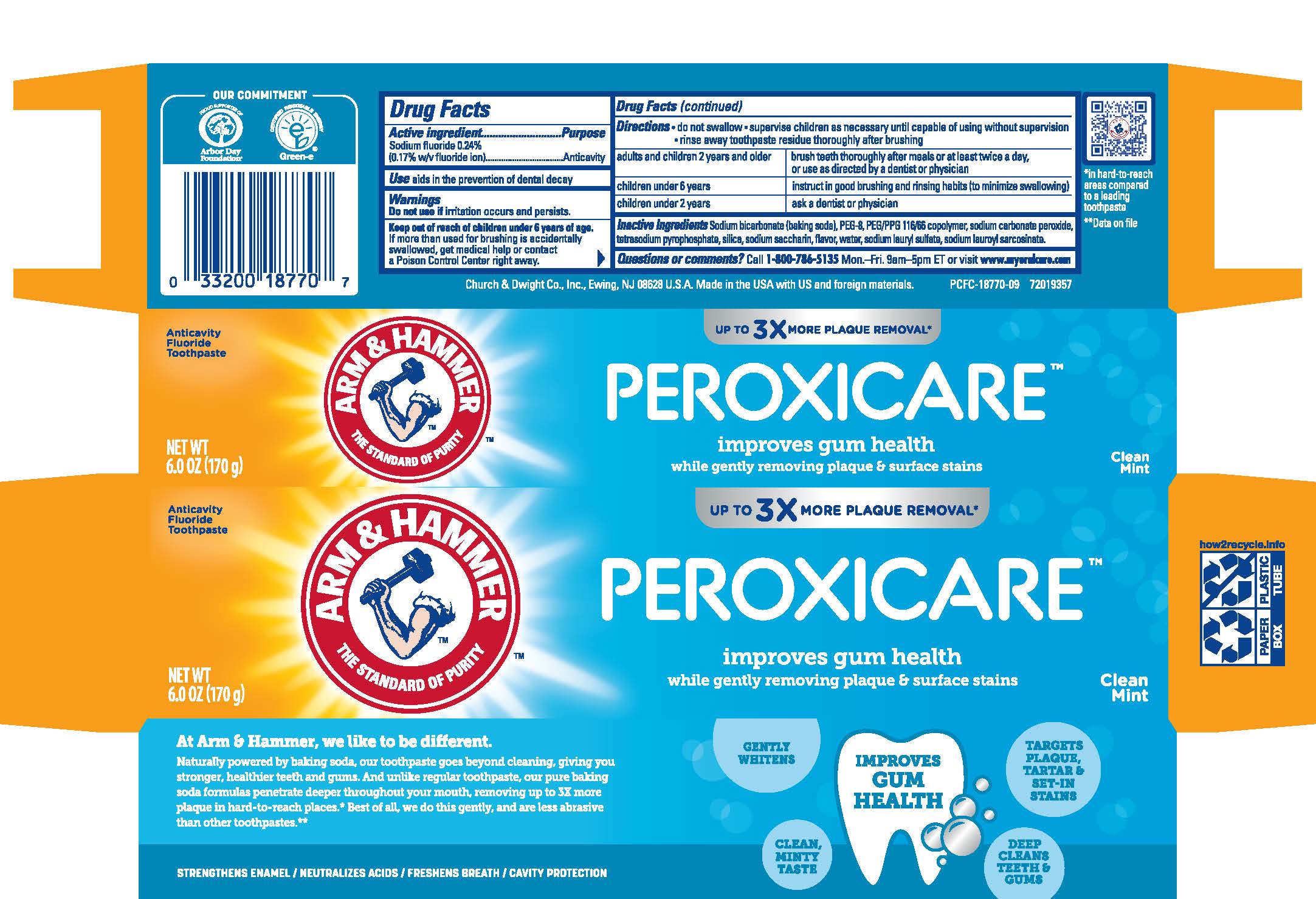 DRUG LABEL: PEROXICARE
NDC: 10237-655 | Form: PASTE, DENTIFRICE
Manufacturer: Church & Dwight Co., Inc.
Category: otc | Type: HUMAN OTC DRUG LABEL
Date: 20251211

ACTIVE INGREDIENTS: SODIUM FLUORIDE 2.4 mg/1 g
INACTIVE INGREDIENTS: SODIUM PYROPHOSPHATE; SODIUM CARBONATE; SILICON DIOXIDE; SACCHARIN SODIUM; WATER; SODIUM LAURYL SULFATE; SODIUM LAUROYL SARCOSINATE; SODIUM BICARBONATE; POLYETHYLENE GLYCOL, UNSPECIFIED

PEROXICARE

Drug Facts

Active ingredient

Sodium fluoride (0.24%)

Purpose

Anticavity

Use

aids in the prevention of dental decay

Warnings

Do not use if irritation occurs and persists.

Keep out of reach of children under 6 years of age.

If more than used for brushing is accidentally swallowed, get medical help or contact a Poison Control Center right away.

Directions

• do not swallow • supervise children as necessary until capable of using without supervision • rinse away toothpaste residue thoroughly after brushing

adults and children 2 years and older | brush teeth throughly after meals or at least twice a day, or use as directed by a dentist or physician
children under 6 years | instruct in good brushing and rinsing habits (to minimize swallowing)
children under 2 years | consult a dentist or physician

Inactive Ingredients

Sodium bicarbonate (baking soda), PEG-8, PEG/PPG-116/66 copolymer, sodium carbonate peroxide, tetrasodium pyrophosphate, silica, sodium saccharin, flavor, water, sodium lauryl sulfate, sodium lauroyl sarcosinate.

Questions or comments?

Call 1-800-786-5135 Mon.-Fri. 9am-5pm ET or visit www.myoralcare.com

Principal Display Panel

Anticavity Fluoride Toothpaste

UP TO 3X MORE PLAQUE REMOVAL in hard-to-reach places

PEROXICARE

improves gum health

while gently removing plaque & surface stains

Clean Mint

NET WT. 6.0 OZ (170 g)